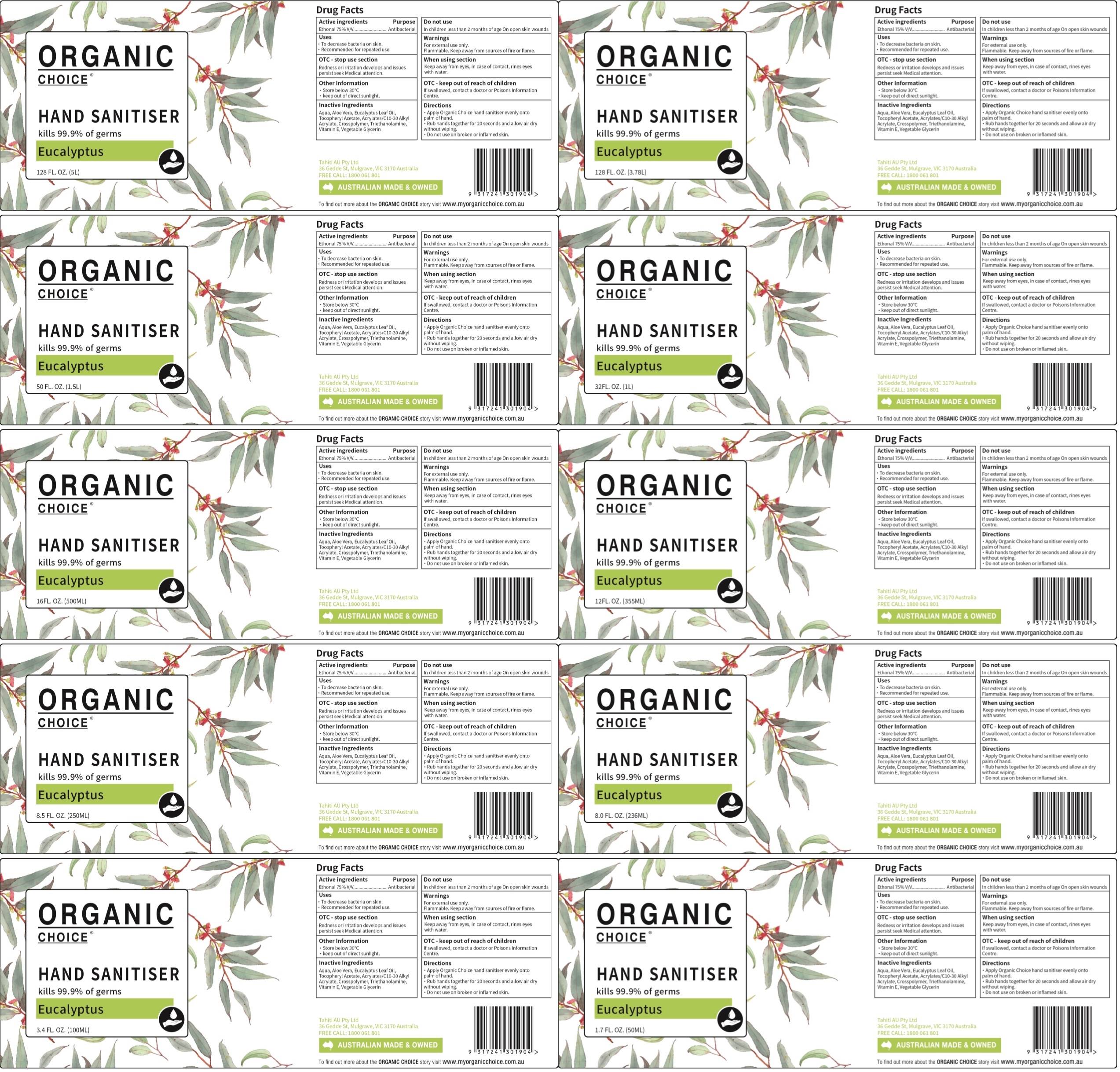 DRUG LABEL: Organic choice hand sanitizer
NDC: 79746-001 | Form: GEL
Manufacturer: TAHITI AU PTY LTD
Category: otc | Type: HUMAN OTC DRUG LABEL
Date: 20200722

ACTIVE INGREDIENTS: ALCOHOL 75 mL/100 mL
INACTIVE INGREDIENTS: TROLAMINE; .ALPHA.-TOCOPHEROL; GLYCERIN; ALOE VERA LEAF; EUCALYPTUS OIL; WATER; .ALPHA.-TOCOPHEROL ACETATE; CARBOMER COPOLYMER TYPE A (ALLYL PENTAERYTHRITOL CROSSLINKED); ADIPIC ACID/DIGLYCOL CROSSPOLYMER (20000 MPA.S)

Organic choice hand sanitizer

Active Ingredient(s)

EthonaI 75% V/v

Purpose

Antibacterial

Use

To decrease bacteria on skin.
Recomm ended for repeated use.

Warnings

For external use only.
Flammable. Keep away from sources of fire or flame.

Do not use

In children less than 2 months of age On open skin wounds

WHEN USING

Keep away from eyes, in case of contact, rines eyes with water.

STOP USE

Redness or irritation develops and issues persist seek Medical attention.

Keep out of reach of children. If swallowed, contact a doctor or Poisons Information Centre.

Directions

Apply Organic Choice hand sanitiser evenly onto palm of hand.
Rub hands together for 20 seconds and allow air dry without wiping.
Do not use on broken or inflamed skin.

Other information

Store below 30°C
keep out of direct sunlight.

Inactive ingredients

Aqua, Aloe Vera, Eucalyptus Leaf Oil, Tocopheryl Acetate, Acrylates/C10-30 Alkyl Acrylate , Crosspolymer, Triethanolamine, Vitamin E , Vegetable Glycerin